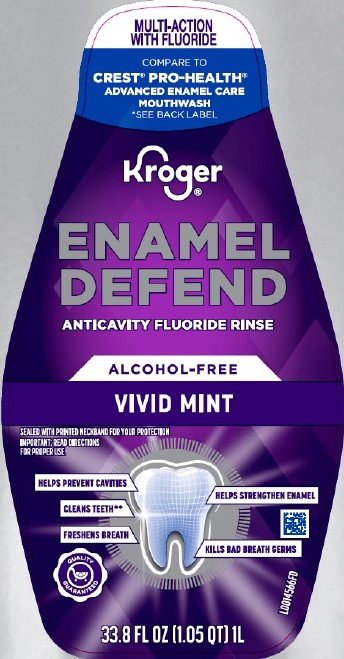 DRUG LABEL: Alcohol-Free Anticavity
NDC: 30142-482 | Form: LIQUID
Manufacturer: The Kroger Co.
Category: otc | Type: HUMAN OTC DRUG LABEL
Date: 20260227

ACTIVE INGREDIENTS: SODIUM FLUORIDE 0.1 mg/1 mL
INACTIVE INGREDIENTS: WATER; GLYCERIN; CETYLPYRIDINIUM CHLORIDE; CINNAMALDEHYDE; SACCHARIN SODIUM; PHOSPHORIC ACID; SODIUM BENZOATE; SUCRALOSE; POLOXAMER 407; BENZOIC ACID; SODIUM PHOSPHATE, DIBASIC, ANHYDROUS; PROPYLENE GLYCOL; D&C RED NO. 33; FD&C GREEN NO. 3

Kroger 482.002/482AC
Alcohol Free Fluoride Violet Mint Mouthwash

Claims

Kroger ®

ENAMEL DEFEND

ANTICAVITY FLUORIDE RINSE

Active ingredient

Sodium fluoride 0.02%

(0.01% w/v fluoride ion)

Purpose

Anticavity

use

aids in the prevention of dental cavities

Warning

For this product

Keep out of reach of children

If more than used for rinsing is accidentally swallowed, get medical help or contact a Poison Control Center right away.

Directions

Adults and children 6 years of age and older:

- use twice daily after brushing your teeth with a toothpaste
- vigorously swish 10 mL (2 teaspoonfuls) of rinse between your teeth for 1 minute then spit out
- do not swallow the rinse
- do not eat or drink for 30 minutes after rinsing
- instruct children under 12 years of age in good rinsing habits (to minimize swallowing)
- supervise children as necessary until capable of using without supervision
- children under 6 years of age: consult a dentist or doctor

Inactive ingredients

water, glycerin, cetylpyridinium chloride, flavor, cinnamal, sodium saccharin, phosphoric acid, sodium benzoate, sucralose, poloxamer 407, benzoic acid, disodium phosphate, propylene glycol, red 33, green 3

Questions or comments?

1-800-632-6900

ADVERSE REACTION

THIS RINSE MAY CAUSE TEMPORARY STAINING TO THE SURFACE OF TEETH.

THIS IS NOT HARMFUL, AND ADEQUATE BRUSHING MAY PREVENT ITS OCCURRENCE.

*THIS PRODUCT IS NOT MANUFACTURED OR DISTRIBUTED BY PROCTER & GAMBLE, DISTRIBUTOR OF CREST ® PRO-HEALTH ® ADVANCED ANITCAVITY FLUORIDE MOUTHWASH ENAMEL CARE ALCOHOL FREE.

**THIS PRODUCT IS NOT INTENDED TO REPLACE BRUSHING OR FLOSSING.

PROUDLY DISTRIBUTED BY THE KROGER CO. CINCINNATI, OHIO 45202

MADE IN USA WITH DOMESTIC AND FOREIGN COMPONENTS

QUALITY GUARANTEED

Quality Guaranteed

Kroger.com/guarantee

800-632-6900

principal display panel

MULTI-ACTION WITH FLUORIDE

COMPARE TO CREST ®PRO-HEALTH ®ADVANCED ENAMEL CARE MOUTHWASH

*SEE BACK LABEL

Kroger ®

ENAMEL DEFEND

ANTICAVITY FLUORIDE RINSE

ALCOHOL-FREE

VIVID MINT

SEALED WITH PRINTED NECKBAND FOR YOUR PROTECTION

IMPORTANT: READ DIRECTIONS FOR PROPER USE.

HELPS PREVENT CAVITIES

CLEANS TEETH**

FRESHENS BREATH

HELPS STRENGTHEN ENAMEL

KILLS BAD BREATH GERMS

QUALITY GUARANTEED

33.8 FL OZ (1.05 QT) 1L